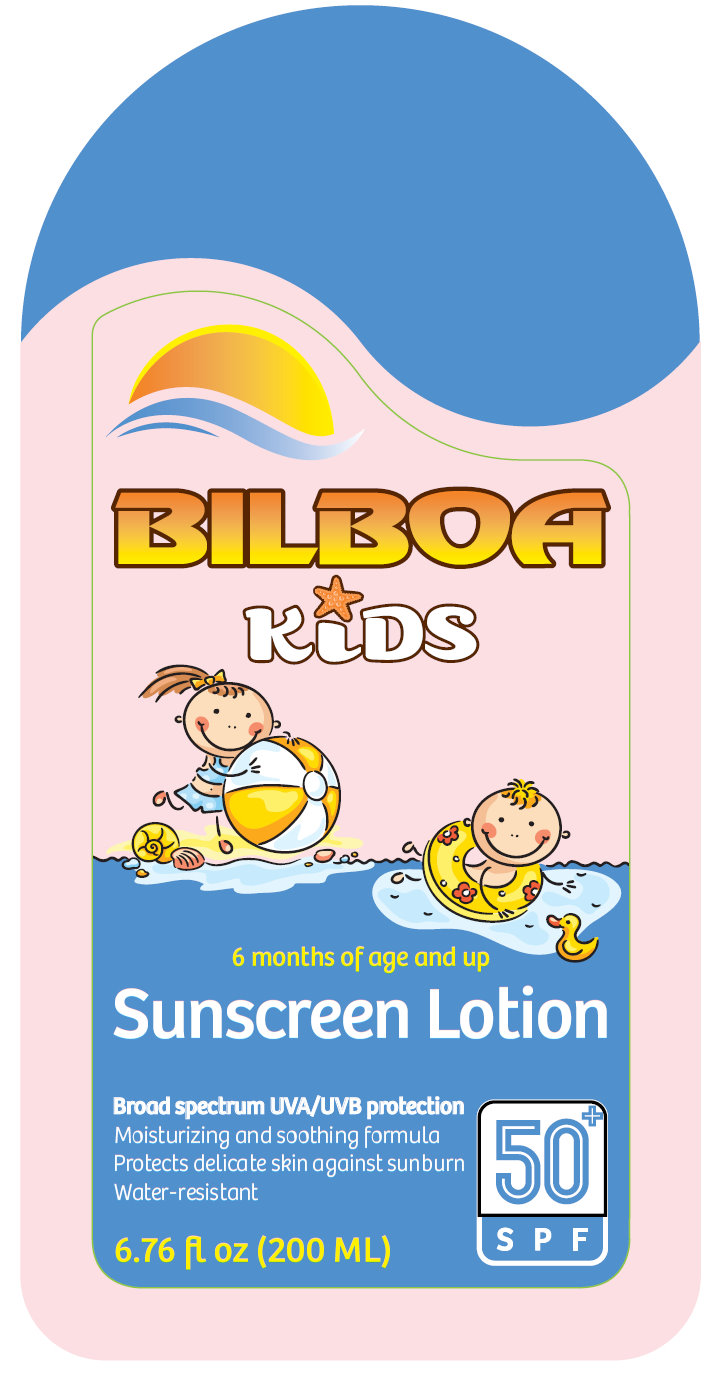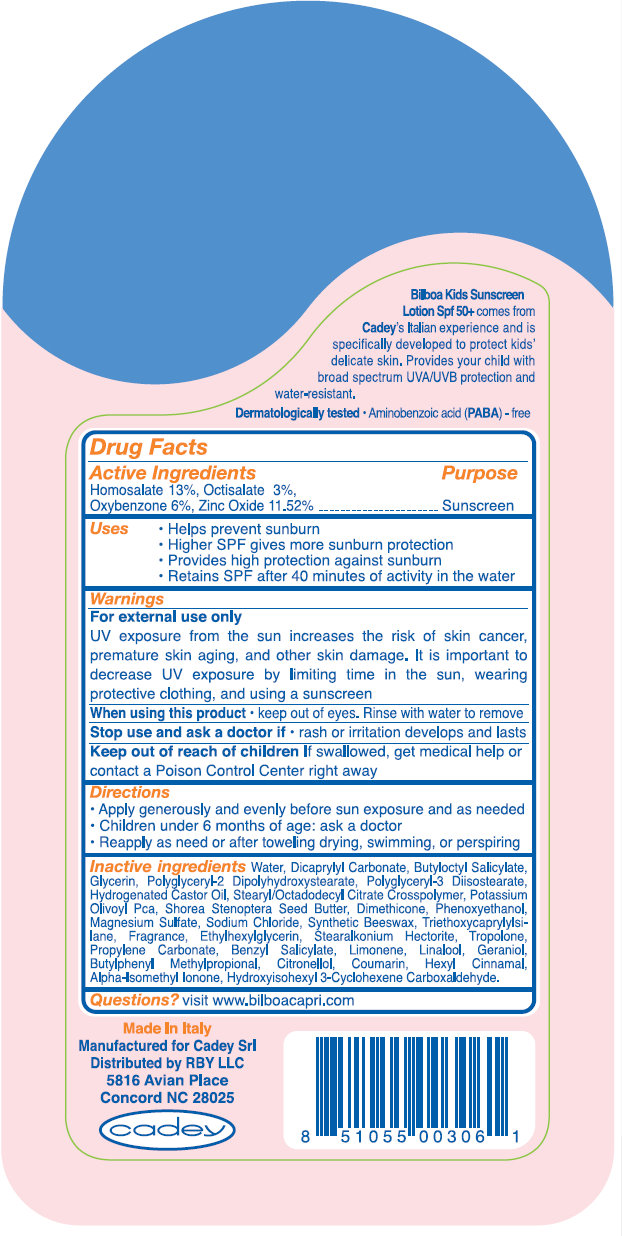 DRUG LABEL: Bilboa Kids Sunscreen SPF 50 Plus
NDC: 76070-130 | Form: LOTION
Manufacturer: Cadey S.r.l.
Category: otc | Type: HUMAN OTC DRUG LABEL
Date: 20110506

ACTIVE INGREDIENTS: HOMOSALATE 13 mL/100 mL; OCTISALATE 3 mL/100 mL; OXYBENZONE 6 mL/100 mL; ZINC OXIDE 11.52 mL/100 mL
INACTIVE INGREDIENTS: WATER; DICAPRYLYL CARBONATE; BUTYLOCTYL SALICYLATE; GLYCERIN; HYDROGENATED CASTOR OIL; DIMETHICONE; PHENOXYETHANOL; MAGNESIUM SULFATE, UNSPECIFIED; SODIUM CHLORIDE; TRIETHOXYCAPRYLYLSILANE; ETHYLHEXYLGLYCERIN; TROPOLONE; PROPYLENE CARBONATE; BENZYL SALICYLATE; LINALOOL, DL-; GERANIOL; BUTYLPHENYL METHYLPROPIONAL; COUMARIN; .ALPHA.-HEXYLCINNAMALDEHYDE; ISOMETHYL-.ALPHA.-IONONE; HYDROXYISOHEXYL 3-CYCLOHEXENE CARBOXALDEHYDE

Bilboa Kids Sunscreen Lotion SPF 50 Plus

Active Ingredients Purpose

Homosalate 13%, Octisalate 3%,
Oxybenzone 6%, Zinc Oxide 11.52% Sunscreen

Uses
- Helps prevent sunburn
- Higher SPF gives more sunburn protection
- Provides high protection against sunburn
- Retains SPF after 40 minutes of activity in the water

Warnings
For external use only

UV exposure from the sun increases the risk of skin cancer, premature skin aging, and other skin damage. It is important to decrease UV exposure by limiting time in the sun, wearing protective clothing, and using a sunscreen

When using this product - keep out of eyes. Rinse with water to remove

Stop use and ask a doctor if - rash or irritation develops and lasts

Keep out of reach of children If swallowed, get medical help or contact a Poison Control Center right away

Directions
- Apply generously and evenly before sun exposure and as needed
- Children under 6 months of age: ask a doctor
- Reapply as need or after toweling drying, swimming, or perspiring

INACTIVE INGREDIENT

Inactive ingredients Water, Dicaprylyl Carbonate, Butyloctyl Salicylate, Glycerin, Polyglyceryl-2 Dipolyhydroxystearate, Polyglyceryl-3 Diisostearate, Hydrogenated Castor Oil, Stearyl/Octadodecyl Citrate Crosspolymer, Potassium Olivoyl Pca, Shorea Stenoptera Seed Butter, Dimethicone, Phenoxyethanol, Magnesium Sulfate, Sodium Chloride, Synthetic Beeswax, Triethoxycaprylylsilane, Fragrance, Ethylhexylglycerin, Stearalkonium Hectorite, Tropolone, Propylene Carbonate, Benzyl Salicylate, Limonene, Linalool, Geraniol, Butylphenyl Methylpropional, Citronellol, Coumarin, Hexyl Cinnamal, Alpha-Isomethyl Ionone, Hydroxyisohexyl 3-Cyclohexene Carboxaldehyde.

Questions? visit www.cadeyusa.com

DESCRIPTION

Bilboa Kids Sunscreen Lotion Spf 50+ comes from Cadey’s Italian experience and is specifically developed to protect kids’ delicate skin. Provides your child with broad spectrum UVA/UVB protection and water-resistant. Dermatologically tested - Aminobenzoic acid (PABA) - free

Made In Italy
Manufactured for Cadey Srl
Distributed by RBY LLC
5816 Avian Place
Concord NC 28025

cadey

PACKAGE LABEL

BILBOA KIDS 6 months of age and up Sunscreen Lotion Broad spectrum UVA/UVB protection Moisturizing and soothing formula Protects delicate skin against sunburn 50+ SPF Water-resistant 6.76 fl oz (200 ML) Made In Italy Manufactured for Cadey Srl Distributed by RBY LLC 5816 Avian Place Concord NC 28025 cadey 8 51055 00306 1